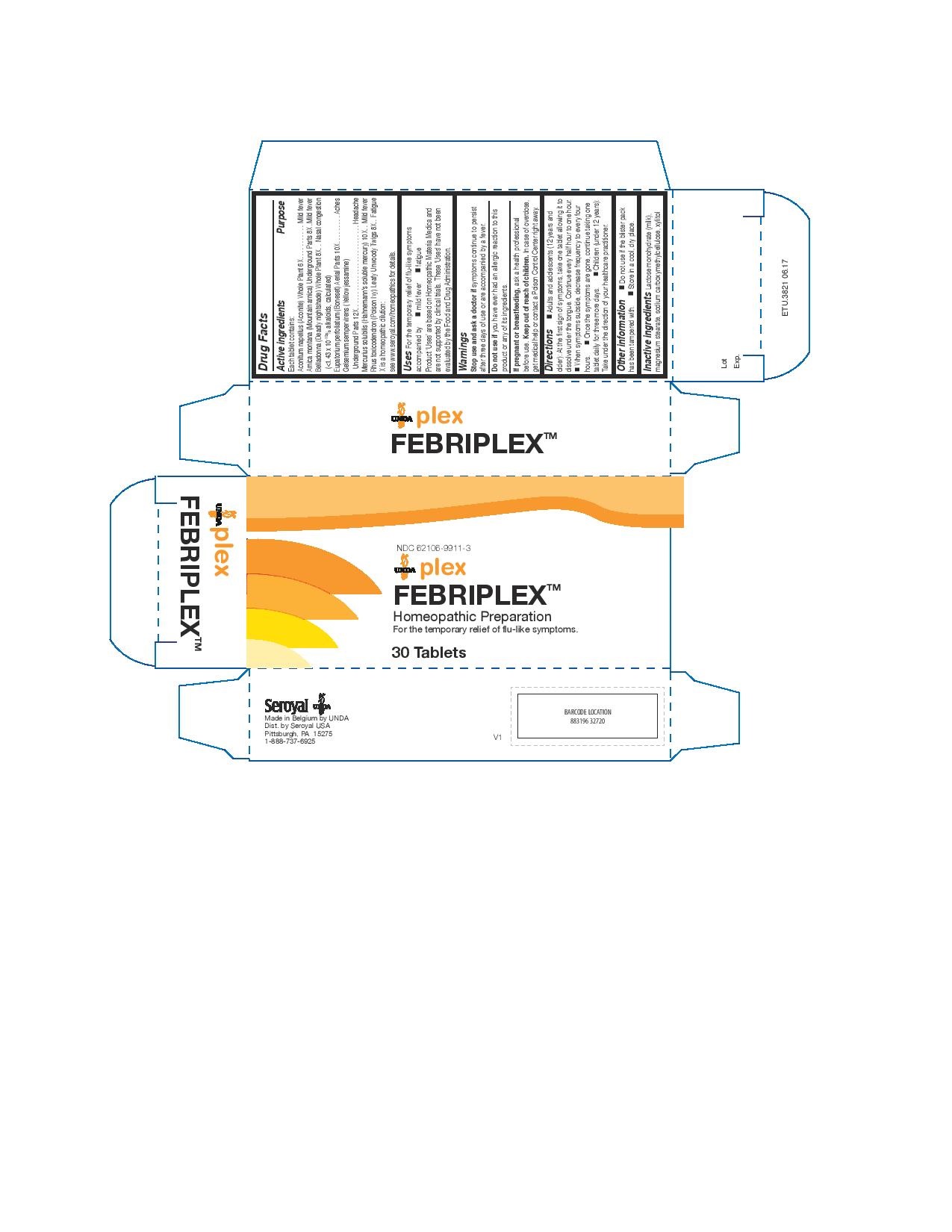 DRUG LABEL: FEBRIPLEX
NDC: 62106-9911 | Form: TABLET
Manufacturer: Seroyal USA
Category: homeopathic | Type: HUMAN OTC DRUG LABEL
Date: 20221107

ACTIVE INGREDIENTS: ACONITUM NAPELLUS 6 [hp_X]/1 1; ARNICA MONTANA ROOT 8 [hp_X]/1 1; ATROPA BELLADONNA 8 [hp_X]/1 1; EUPATORIUM PERFOLIATUM FLOWERING TOP 10 [hp_X]/1 1; GELSEMIUM SEMPERVIRENS ROOT 12 [hp_X]/1 1; MERCURIUS SOLUBILIS 10 [hp_X]/1 1; TOXICODENDRON PUBESCENS SHOOT 8 [hp_X]/1 1
INACTIVE INGREDIENTS: LACTOSE MONOHYDRATE; MAGNESIUM STEARATE; CARBOXYMETHYLCELLULOSE SODIUM; XYLITOL

FEBRIPLEX

Active ingredients
Each tablet contains:
Aconitum napellus (Aconite) Whole Plant 6X
Arnica montana (Mountain arnica) Underground Parts 8X
Belladonna (Deadly nightshade) Whole Plant 8X
(<1.43 x 10-10% alkaloids, calculated)
Eupatorium perfoliatum (Boneset) Aerial Parts 10X
Gelsemium sempervirens (Yellow jessamine) Underground Parts 12X
Mercurius solubilis (Hahnemann's soluble mercury) 10X
Rhus toxicodendron (Poison Ivy) Leafy Unwoody Twigs 8X

Uses

For the temporary relief of flu-like symptoms accompanied by mild fever and fatigue.

Warnings
Stop use and ask a doctor if symptoms continue to persist
after three days of use or are accompanied by a fever.
Do not use if you have ever had an allergic reaction to this
product or any of its ingredients.
If pregnant or breastfeeding, ask a health professional
before use. Keep out of reach of children. In case of overdose,
get medical help or contact a Poison Control Center right away.

Keep out of reach of children.

PREGNANCY OR BREAST FEEDING

If pregnant or breastfeeding, ask a health professional before use.

Other information

Do not use if the blister pack has been tampered with.

Store in a cool, dry place.

Inactive ingredients

Lactose monohydrate (milk), magnesium stearate, sodium carboxymethylcellulose, xylitol

Directions

Adults and adolescents (12 years and older):

At the first sign of symptoms, take one tablet allowing it to
dissolve under the tongue. Continue every half hour to one hour.
When symptoms subside, decrease frequency to every four hours.

Once the symptoms are gone, continue taking one tablet daily for three more days.

Children (under 12 years):
Take under the direction of your healthcare practitioner.

Uses

For the temporary relief of flu-like symptoms accompanied by mild fever and fatigue
Directions

Adults and adolescents (12 years and older):

At the first sign of symptoms, take one tablet allowing it to
dissolve under the tongue. Continue every half hour to one hour.
When symptoms subside, decrease frequency to every four hours.

Once the symptoms are gone, continue taking one tablet daily for three more days.

Children (under 12 years):
Take under the direction of your healthcare practitioner.

PACKAGE LABEL

NDC 62106-9911-3

UNDA plex

FEBRIPLEX(TM)

Homeopathic Preparation

For the temporary relief of flu-like symptoms.

30 Tablets